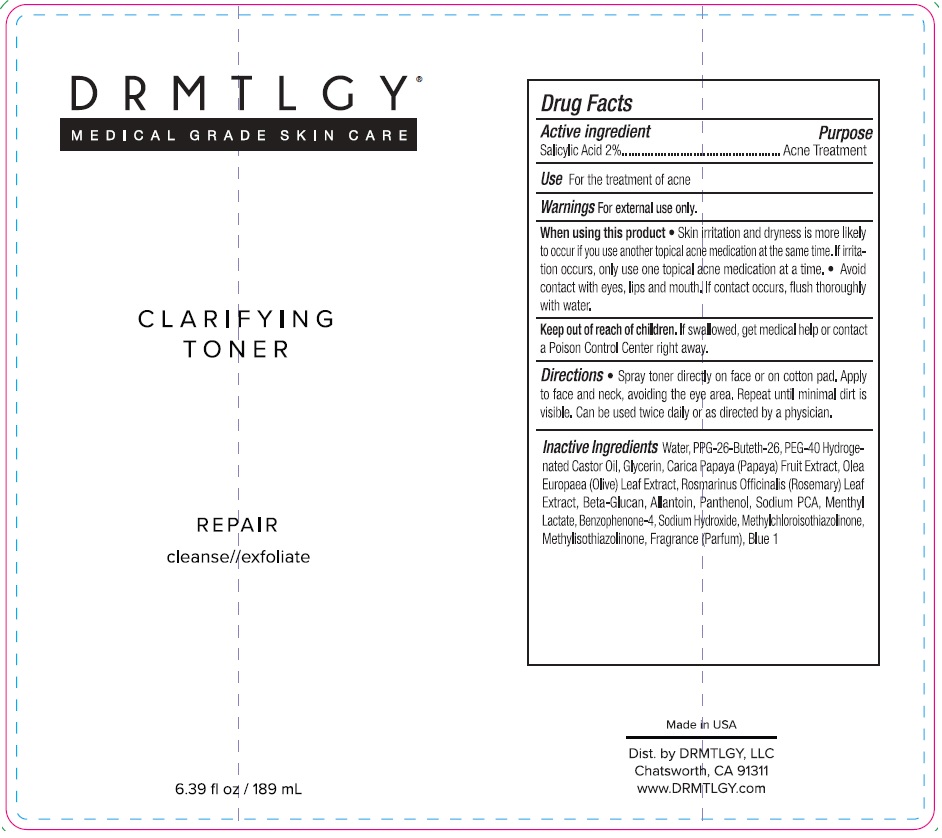 DRUG LABEL: CLARIFYING TONER
NDC: 83286-012 | Form: LIQUID
Manufacturer: Drmtlgy, LLC
Category: otc | Type: HUMAN OTC DRUG LABEL
Date: 20250409

ACTIVE INGREDIENTS: SALICYLIC ACID 2 g/100 mL
INACTIVE INGREDIENTS: WATER; PPG-26-BUTETH-26; POLYOXYL 40 HYDROGENATED CASTOR OIL; GLYCERIN; PAPAYA; OLEA EUROPAEA (OLIVE) LEAF POWDER; ROSEMARY; YEAST .BETA.-D-GLUCAN; ALLANTOIN; PANTHENOL; SODIUM PYRROLIDONE CARBOXYLATE; MENTHYL LACTATE, (-)-; SULISOBENZONE; SODIUM HYDROXIDE; METHYLCHLOROISOTHIAZOLINONE; METHYLISOTHIAZOLINONE; FD&C BLUE NO. 1

DRMTLGY® CLARIFYING TONER

Active ingredient

Salicylic Acid 2%

Purpose

Acne Treatment

Use

For the treatment of acne

Warnings

For external use only.

When using this product • Skin irritation and dryness is more likely to occur if you use another topical acne medication at the same time. If irritation occurs, only use one topical acne medication at a time. • Avoid contact with eyes, lips and mouth. If contact occurs, flush thoroughly with water.

Keep out of reach of children. If swallowed, get medical help or contact a Poison Control Center right away.

Directions

• Spray toner directly on face or on cotton pad. Apply to face and neck, avoiding the eye area. Repeat until minimal dirt is visible. Can be used twice daily or as directed by a physician.

Inactive ingredients

Water, PPG-26-Buteth-26, PEG-40 Hydrogenated Castor Oil, Glycerin, Carica Papaya (Papaya) Fruit Extract, Olea Europaea (Olive) Leaf Extract, Rosmarinus Officinalis (Rosemary) Leaf Extract, Beta-Glucan, Allantoin, Panthenol, Sodium PCA, Menthyl Lactate, Benzophenone-4, Sodium Hydroxide, Methylchloroisothiazolinone, Methylisothiazolinone, Fragrance (Parfum), Blue 1

MEDICAL GRADE SKIN CARE

REPAIR

cleanse//exfoliate

Made in USA

Dist. by DRMTLGY, LLC
Chatsworth, CA 91311
www.DRMTLGY.com